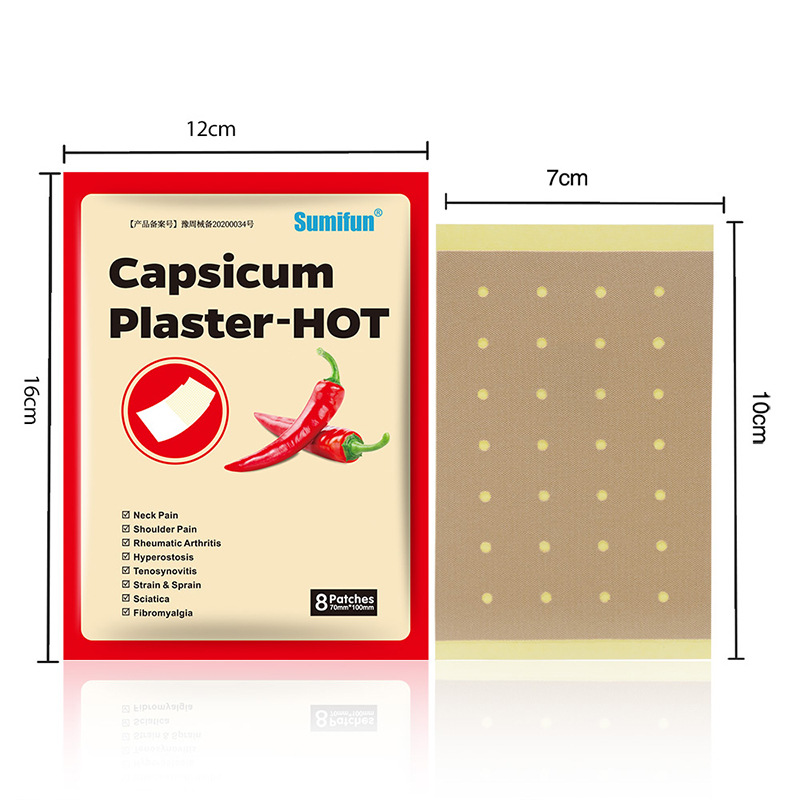 DRUG LABEL: Capsicum Plaster-HOT
NDC: 83675-016 | Form: PATCH
Manufacturer: Guangzhou Hanhai Trading Co., Ltd
Category: otc | Type: HUMAN OTC DRUG LABEL
Date: 20231007

ACTIVE INGREDIENTS: CAPSICUM 12 g/100 1
INACTIVE INGREDIENTS: CAMPHOR (NATURAL); MENTHOL, (+)-

Active Ingredient

Capsicum Extract 12.0%

Purpose

Relieve Pain

Use

Help relieve pain

Warnings

For external use only.

Keep Out Of Reach Of Children
Pregnant, breast-feeding, people with severe chronic diseases or allergic to the raw materials are forbidden to use

Do not use

Product shall not be eat

When Using

Do not stick around eyes and mouth,This product cannot replace drugs.

Stop Use

In case of adverse reactions, please stop using this product.If the symptoms.

Ask Doctor

ask doctor in case of adverse reactions

Keep Oot Of Reach Of Children

Keep Out Of Reach Of Children

Directions

After cleaning and drying the affected area, open the package to remove the back of the paper,
Tear the silicone oil paper andstick it where you want to relief.
Smooth out the pain relief patches so that it fits your skin without wrinkles.

Other information

Store the product in a cool, dry and well-ventilated place

Avoid direct sunlight

Inactive ingredients

Camphor
Menthol